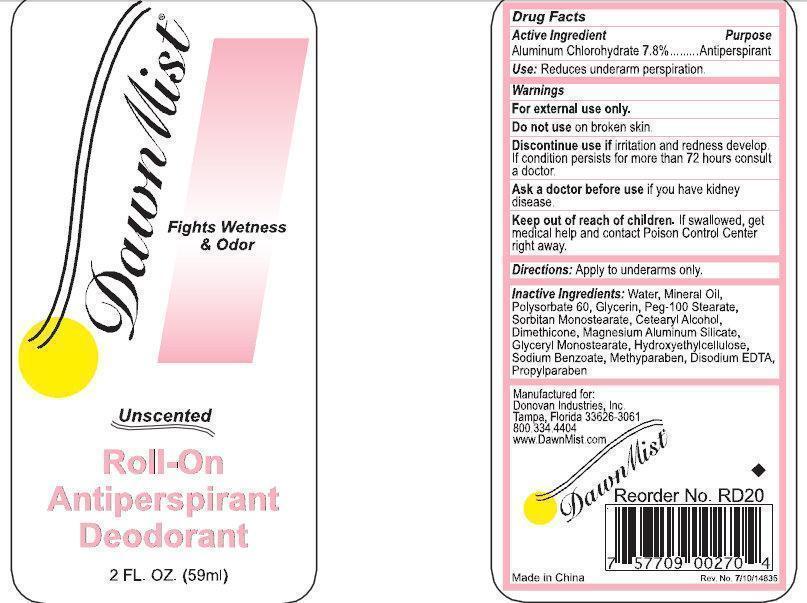 DRUG LABEL: DawnMist Unscented Roll-On Antiperspirant Deodorant
                        
NDC: 55504-9002 | Form: SOLUTION
Manufacturer: Donovan Industries, Inc.
Category: otc | Type: HUMAN OTC DRUG LABEL
Date: 20150717

ACTIVE INGREDIENTS: ALUMINUM CHLOROHYDRATE 78 mg/100 mL
INACTIVE INGREDIENTS: WATER; MINERAL OIL; POLYSORBATE 60; GLYCERIN; POLYOXYL 100 STEARATE; SORBITAN MONOSTEARATE; CETOSTEARYL ALCOHOL; DIMETHICONE; MAGNESIUM ALUMINUM SILICATE; GLYCERYL MONOSTEARATE; SODIUM BENZOATE; METHYLPARABEN; EDETATE DISODIUM; PROPYLPARABEN

DawnMist Unscented Roll-On Antiperspirant Deodorant

Active Ingredient

Aluminum Chlorohydrate 7.8%

Purpose

Antiperspirant

INDICATIONS AND USAGE

Use: Reduces underarm perspiration

Warnings

For external use only.
Do not use on broken skin.
Discontinue use if irritation and redness develop. If condition persists for more than 72 hours consult a doctor.
Ask a doctor before use if you have kidney disease.

Keep out of reach of children. If swallowed, get medical help and contact Poison Control Center right away.

DOSAGE AND ADMINISTRATION

Directions: Apply to underarms only.

INACTIVE INGREDIENT

Inactive Ingredients: Water, Mineral Oil, Polysorbate 60, Glycerin, Peg-100 Stearate, Sorbitan Monostearate, Ceteraryl Alcohol, Dimethicone, Magnesium Aluminum Silicate, Glyceryl Monostearate, Hydroxyethylcellulose, Sodium Benzoate, Methylparaben, Disodium EDTA, Propylparaben

Manufactured for:

Donovan Industries, Inc.

Tampa, Florida 33626-3061

800.334.4404

www.DawnMist.com

Made in China

PACKAGE LABEL

DawnMist

Fights Wetness and Odor

Unscented

Roll-On

Antiperspirant

Deodorant

2 FL. OZ 59ml